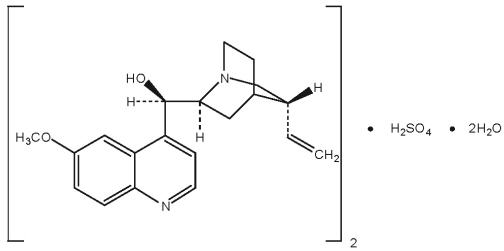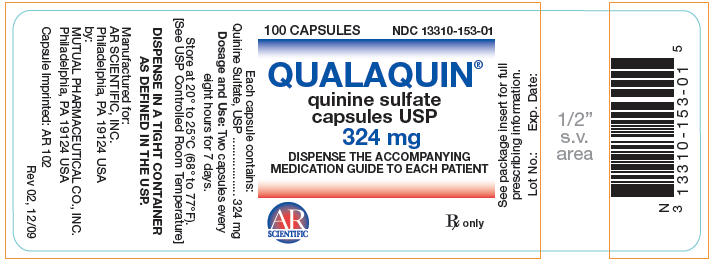 DRUG LABEL: Qualaquin
NDC: 13310-153 | Form: CAPSULE
Manufacturer: AR Scientific Inc.
Category: prescription | Type: HUMAN PRESCRIPTION DRUG LABEL
Date: 20130423

ACTIVE INGREDIENTS: Quinine Sulfate 324 mg/1 1
INACTIVE INGREDIENTS: starch, corn; magnesium stearate; talc

HIGHLIGHTS OF PRESCRIBING INFORMATION

These highlights do not include all the information needed to use QUALAQUIN® safely and effectively. See full prescribing information for QUALAQUIN®.
QUALAQUIN® (quinine sulfate) Capsules, USP for Oral use
Initial U.S. Approval: 2005
BOXED WARNING (See full prescribing information for complete boxed warning)

WARNING:

QUALAQUIN® use for the treatment or prevention of nocturnal leg cramps may result in serious and life-threatening hematologic reactions, including thrombocytopenia and hemolytic uremic syndrome/thrombotic thrombocytopenic purpura (HUS/TTP). Chronic renal impairment associated with the development of TTP has been reported. The risk associated with QUALAQUIN use in the absence of evidence of its effectiveness in the treatment or prevention of nocturnal leg cramps outweighs any potential benefit (see WARNINGS).

RECENT MAJOR CHANGES

Dose and Administration
Hepatic Impairment (2.3) | 4/2013
Warnings and Precautions
QT Prolongation and Ventricular Arrhythmias (5.3) | 9/2012

1 INDICATIONS AND USAGE

QUALAQUIN® (quinine sulfate) is a cinchona alkaloid indicated for treatment of uncomplicated Plasmodium falciparum malaria (1).

2 DOSAGE AND ADMINISTRATION

- Adults (≥ 16 years of age): 648 mg (two capsules) every 8 hours for 7 days (2.1).
- Patients with severe chronic renal impairment: one loading dose of 648 mg (two capsules) followed 12 hours later by 324 mg (one capsule) every 12 hours for 7 days (2.2).

3 DOSAGE FORMS AND STRENGTHS

- 324 mg hard gelatin, clear cap/clear body capsules, imprinted with 'AR 102' (3).

4 CONTRAINDICATIONS

QUALAQUIN is contraindicated in patients with the following:

- Prolongation of QT interval (4)
- Glucose-6-phosphate dehydrogenase (G6PD) deficiency (4)
- Myasthenia gravis (4)
- Known hypersensitivity to quinine, mefloquine, or quinidine (4)
- Optic neuritis (4)

5 WARNINGS AND PRECAUTIONS

- Not indicated for the prevention or treatment of nocturnal leg cramps. Risk of serious and life-threatening adverse reactions (1, 5.1).
- Thrombocytopenia, including ITP and HUS/TTP, has been reported. Discontinue drug (5.2).
- QT prolongation and ventricular arrhythmias. Avoid concomitant use with drugs known to prolong QT interval (5.3).
- Avoid concomitant use with rifampin. QUALAQUIN treatment failures have been reported (5.4).
- Avoid concomitant use with neuromuscular blocking agents. QUALAQUIN may potentiate neuromuscular blockade and cause respiratory depression (5.5).
- Serious and life threatening hypersensitivity reactions. Discontinue drug (4, 5.6).
- Atrial fibrillation and flutter. Paradoxical increase in ventricular rate may occur. Closely monitor digoxin levels if used concomitantly (5.7).
- Hypoglycemia. Monitor for signs and symptoms (5.8).

6 ADVERSE REACTIONS

Most common adverse reactions are a cluster of symptoms called "cinchonism", which occurs to some degree in almost all patients taking quinine: headache, vasodilation and sweating, nausea, tinnitus, hearing impairment, vertigo or dizziness, blurred vision, disturbance in color perception, vomiting, diarrhea, abdominal pain, deafness, blindness, and disturbances in cardiac rhythm or conduction (6.1).
To report SUSPECTED ADVERSE REACTIONS, contact Mutual Pharmaceutical Company, Inc. at 1-888-351-3786 or drugsafety@urlpharma.com or FDA at 1-800-FDA-1088 or www.fda.gov/medwatch.

7 DRUG INTERACTIONS

Interacting Drug | Interaction
Drugs known to prolong QT interval (e.g., Class IA and Class III antiarrhythmic agents). | QUALAQUIN prolongs QT interval, ECG abnormalities including QT prolongation and Torsades de Pointes. Avoid concomitant use (5.3).
Other antimalarials (e.g., halofantrine, mefloquine). | ECG abnormalities including QT prolongation. Avoid concomitant use (5.3, 7.2).
CYP3A4 inducers or inhibitors | Alteration in plasma quinine concentration. Monitor for lack of efficacy or increased adverse events of quinine (7.1).
CYP3A4 and CYP2D6 substrates | Quinine is an inhibitor of CYP3A4 and CYP2D6. Monitor for lack of efficacy or increased adverse events of the co-administered drug (7.2).
Digoxin | Increased digoxin plasma concentration (5.8, 7.1).

See full prescribing information for a complete list of reported and potential interactions.

8 USE IN SPECIFIC POPULATIONS

- Renal impairment: Reduce dose and dosing frequency for patients with severe chronic renal impairment (2.2, 8.6, 12.3).
- Hepatic impairment: Closely monitor for adverse events. Quinine should not be administered in patients with severe (Child-Pugh C) hepatic impairment (2.3, 8.7, 12.3).
- Pregnancy: Based on animal data may cause fetal harm. Use only if the potential benefit justifies the risk (8.1).
- Nursing Mothers: Exercise caution when administering to a nursing woman (8.3).

FULL PRESCRIBING INFORMATION

WARNING:

QUALAQUIN® use for the treatment or prevention of nocturnal leg cramps may result in serious and life-threatening hematologic reactions, including thrombocytopenia and hemolytic uremic syndrome/thrombotic thrombocytopenic purpura (HUS/TTP). Chronic renal impairment associated with the development of TTP has been reported. The risk associated with QUALAQUIN use in the absence of evidence of its effectiveness in the treatment or prevention of nocturnal leg cramps outweighs any potential benefit (see WARNINGS).

1 INDICATIONS AND USAGE

QUALAQUIN (quinine sulfate) is an antimalarial drug indicated only for treatment of uncomplicated Plasmodium falciparum malaria. Quinine sulfate has been shown to be effective in geographical regions where resistance to chloroquine has been documented [see Clinical Studies (14)].

QUALAQUIN oral capsules are not approved for:

- Treatment of severe or complicated P. falciparum malaria.
- Prevention of malaria.
- Treatment or prevention of nocturnal leg cramps [see Warnings and Precautions (5.1)].

2 DOSAGE AND ADMINISTRATION

2.1 Treatment of Uncomplicated P. falciparum Malaria

For treatment of uncomplicated P. falciparum malaria in adults: Orally, 648 mg (two capsules) every 8 hours for 7 days [see Clinical Studies (14)].

QUALAQUIN should be taken with food to minimize gastric upset [see Clinical Pharmacology (12.3)].

2.2 Renal Impairment

In patients with acute uncomplicated malaria and severe chronic renal impairment, the following dosage regimen is recommended: one loading dose of 648 mg QUALAQUIN followed 12 hours later by maintenance doses of 324 mg every 12 hours.

The effects of mild and moderate renal impairment on the safety and pharmacokinetics of quinine sulfate are not known [see Use in Specific Populations (8.6), Clinical Pharmacology (12.3)].

2.3 Hepatic Impairment

Adjustment of the recommended dose is not required in mild (Child-Pugh A) or moderate (Child-Pugh B) hepatic impairment, but patients should be monitored closely for adverse effects of quinine. Quinine should not be administered in patients with severe (Child-Pugh C) hepatic impairment [see Use in Specific Populations (8.7), Clinical Pharmacology (12.3)].

3 DOSAGE FORMS AND STRENGTHS

324 mg capsules - hard gelatin, clear cap/clear body, imprinted with 'AR 102'

4 CONTRAINDICATIONS

QUALAQUIN is contraindicated in patients with the following:

- Prolonged QT interval. One case of a fatal ventricular arrhythmia was reported in an elderly patient with a prolonged QT interval at baseline, who received quinine sulfate intravenously for P. falciparum malaria [see Warnings and Precautions (5.3)].
- Glucose-6-phosphate dehydrogenase (G6PD) deficiency.
- Hemolysis can occur in patients with G6PD deficiency receiving quinine.
- Known hypersensitivity reactions to quinine.
  - These include, but are not limited to, the following [see Warnings and Precautions (5.6)]:
    - Thrombocytopenia
    - Idiopathic thrombocytopenia purpura (ITP) and Thrombotic thrombocytopenic purpura (TTP)
    - Hemolytic uremic syndrome (HUS)
    - Blackwater fever (acute intravascular hemolysis, hemoglobinuria, and hemoglobinemia)
- Known hypersensitivity to mefloquine or quinidine: cross-sensitivity to quinine has been documented [see Warnings and Precautions (5.6)].
  - Myasthenia gravis. Quinine has neuromuscular blocking activity, and may exacerbate muscle weakness.
  - Optic neuritis. Quinine may exacerbate active optic neuritis [see Adverse Reactions (6)].

5 WARNINGS AND PRECAUTIONS

5.1 Use of QUALAQUIN for Treatment or Prevention of Nocturnal Leg Cramps

QUALAQUIN may cause unpredictable serious and life-threatening hematologic reactions including thrombocytopenia and hemolytic-uremic syndrome/thrombotic thrombocytopenic purpura (HUS/TTP) in addition to hypersensitivity reactions, QT prolongation, serious cardiac arrhythmias including torsades de pointes, and other serious adverse events requiring medical intervention and hospitalization. Chronic renal impairment associated with the development of TTP, and fatalities have also been reported. The risk associated with the use of QUALAQUIN in the absence of evidence of its effectiveness for treatment or prevention of nocturnal leg cramps, outweighs any potential benefit in treating and/or preventing this benign, self-limiting condition [see Boxed Warning and Contraindications (4)].

5.2 Thrombocytopenia

Quinine-induced thrombocytopenia is an immune-mediated disorder. Severe cases of thrombocytopenia that are fatal or life threatening have been reported, including cases of HUS/TTP. Chronic renal impairment associated with the development of TTP has also been reported. Thrombocytopenia usually resolves within a week upon discontinuation of quinine. If quinine is not stopped, a patient is at risk for fatal hemorrhage. Upon re-exposure to quinine from any source, a patient with quinine-dependent antibodies could develop thrombocytopenia that is more rapid in onset and more severe than the original episode.

5.3 QT Prolongation and Ventricular Arrhythmias

QT interval prolongation has been a consistent finding in studies which evaluated electrocardiographic changes with oral or parenteral quinine administration, regardless of age, clinical status, or severity of disease. The maximum increase in QT interval has been shown to correspond with peak quinine plasma concentration [see Clinical Pharmacology (12.2)]. Quinine sulfate has been rarely associated with potentially fatal cardiac arrhythmias, including torsades de pointes, and ventricular fibrillation.

QUALAQUIN has been shown to cause concentration-dependent prolongation of the PR and QRS interval. At particular risk are patients with underlying structural heart disease and preexisting conduction system abnormalities, elderly patients with sick sinus syndrome, patients with atrial fibrillation with slow ventricular response, patients with myocardial ischemia or patients receiving drugs known to prolong the PR interval (e.g. verapamil) or QRS interval (e.g. flecainide or quinidine) [see Clinical Pharmacology (12.2)].

QUALAQUIN is not recommended for use with other drugs known to cause QT prolongation, including Class IA antiarrhythmic agents (e.g., quinidine, procainamide, disopyramide), and Class III antiarrhythmic agents (e.g., amiodarone, sotalol, dofetilide).

The use of macrolide antibiotics such as erythromycin should be avoided in patients receiving QUALAQUIN. Fatal torsades de pointes was reported in an elderly patient who received concomitant quinine, erythromycin, and dopamine. Although a causal relationship between a specific drug and the arrhythmia was not established in this case, erythromycin is a CYP3A4 inhibitor and has been shown to increase quinine plasma levels when used concomitantly. A related macrolide antibiotic, troleandomycin, has also been shown to increase quinine exposure in a pharmacokinetic study [see Drug Interactions (7.1)].

Quinine may inhibit the metabolism of certain drugs that are CYP3A4 substrates and are known to cause QT prolongation, e.g., astemizole, cisapride, terfenadine, pimozide, halofantrine and quinidine. Torsades de pointes has been reported in patients who received concomitant quinine and astemizole. Therefore, concurrent use of QUALAQUIN with these medications, or drugs with similar properties, should be avoided [see Drug Interactions (7.2)].

Concomitant administration of QUALAQUIN with the antimalarial drugs, mefloquine or halofantrine, may result in electrocardiographic abnormalities, including QT prolongation, and increase the risk for torsades de pointes or other serious ventricular arrhythmias. Concurrent use of QUALAQUIN and mefloquine may also increase the risk of seizures [see Drug Interactions (7.2)].

QUALAQUIN should also be avoided in patients with known prolongation of QT interval and in patients with clinical conditions known to prolong the QT interval, such as uncorrected hypokalemia, bradycardia, and certain cardiac conditions [see Contraindications (4)].

5.4 Concomitant Use of Rifampin

Treatment failures may result from the concurrent use of rifampin with QUALAQUIN, due to decreased plasma concentrations of quinine, and concomitant use of these medications should be avoided [see Drug Interactions (7.1)].

5.5 Concomitant Use of Neuromuscular Blocking Agents

The use of neuromuscular blocking agents should be avoided in patients receiving QUALAQUIN. In one patient who received pancuronium during an operative procedure, subsequent administration of quinine resulted in respiratory depression and apnea. Although there are no clinical reports with succinylcholine or tubocurarine, quinine may also potentiate neuromuscular blockade when used with these drugs [see Drug Interactions (7.2)].

5.6 Hypersensitivity

Serious hypersensitivity reactions reported with quinine sulfate include anaphylactic shock, anaphylactoid reactions, urticaria, serious skin rashes, including Stevens-Johnson syndrome and toxic epidermal necrolysis, angioedema, facial edema, bronchospasm, and pruritus.

A number of other serious adverse reactions reported with quinine, including thrombotic thrombocytopenic purpura (TTP) and hemolytic uremic syndrome (HUS), thrombocytopenia, immune thrombocytopenic purpura (ITP), blackwater fever, disseminated intravascular coagulation, leukopenia, neutropenia, granulomatous hepatitis, and acute interstitial nephritis may also be due to hypersensitivity reactions.

QUALAQUIN should be discontinued in case of any signs or symptoms of hypersensitivity [see Contraindications (4)].

5.7 Atrial Fibrillation and Flutter

QUALAQUIN should be used with caution in patients with atrial fibrillation or atrial flutter. A paradoxical increase in ventricular response rate may occur with quinine, similar to that observed with quinidine. If digoxin is used to prevent a rapid ventricular response, serum digoxin levels should be closely monitored, because digoxin levels may be increased with use of quinine [see Drug Interactions (7.2)].

5.8 Hypoglycemia

Quinine stimulates release of insulin from the pancreas, and patients, especially pregnant women, may experience clinically significant hypoglycemia.

6 ADVERSE REACTIONS

6.1 Overall

Quinine can adversely affect almost every body system. The most common adverse events associated with quinine use are a cluster of symptoms called "cinchonism", which occurs to some degree in almost all patients taking quinine. Symptoms of mild cinchonism include headache, vasodilation and sweating, nausea, tinnitus, hearing impairment, vertigo or dizziness, blurred vision, and disturbance in color perception. More severe symptoms of cinchonism are vomiting, diarrhea, abdominal pain, deafness, blindness, and disturbances in cardiac rhythm or conduction. Most symptoms of cinchonism are reversible and resolve with discontinuation of quinine.

The following ADVERSE REACTIONS have been reported with quinine sulfate. Most of these reactions are thought to be uncommon, but the actual incidence is unknown:

General: fever, chills, sweating, flushing, asthenia, lupus-like syndrome, and hypersensitivity reactions.

Hematologic: agranulocytosis, hypoprothrombinemia, thrombocytopenia, disseminated intravascular coagulation, hemolytic anemia; hemolytic uremic syndrome, thrombotic thrombocytopenic purpura, idiopathic thrombocytopenic purpura, petechiae, ecchymosis, hemorrhage, coagulopathy, blackwater fever, leukopenia, neutropenia, pancytopenia, aplastic anemia, and lupus anticoagulant.

Neuropsychiatric: headache, diplopia, confusion, altered mental status, seizures, coma, disorientation, tremors, restlessness, ataxia, acute dystonic reaction, aphasia, and suicide.

Dermatologic: cutaneous rashes, including urticarial, papular, or scarlatinal rashes, pruritus, bullous dermatitis, exfoliative dermatitis, erythema multiforme, Stevens-Johnson syndrome, toxic epidermal necrolysis, fixed drug eruption, photosensitivity reactions, allergic contact dermatitis, acral necrosis, and cutaneous vasculitis.

Respiratory: asthma, dyspnea, pulmonary edema.

Cardiovascular: chest pain, vasodilatation, hypotension, postural hypotension, tachycardia, bradycardia, palpitations, syncope, atrioventricular block, atrial fibrillation, irregular rhythm, unifocal premature ventricular contractions, nodal escape beats, U waves, QT prolongation, ventricular fibrillation, ventricular tachycardia, torsades de pointes, and cardiac arrest.

Gastrointestinal: nausea, vomiting, diarrhea, abdominal pain, gastric irritation, and esophagitis.

Hepatobiliary: granulomatous hepatitis, hepatitis, jaundice, and abnormal liver function tests.

Metabolic: hypoglycemia and anorexia.

Musculoskeletal: myalgias and muscle weakness.

Renal: hemoglobinuria, renal failure, renal impairment, and acute interstitial nephritis.

Special Senses: visual disturbances, including blurred vision with scotomata, sudden loss of vision, photophobia, diplopia, night blindness, diminished visual fields, fixed pupillary dilatation, disturbed color vision, optic neuritis, blindness, vertigo, tinnitus, hearing impairment, and deafness.

7 DRUG INTERACTIONS

7.1 Effects of Drugs and Other Substances on Quinine Pharmacokinetics

Quinine is a P-gp substrate and is primarily metabolized by CYP3A4. Other enzymes, including CYP1A2, CYP2C8, CYP2C9, CYP2C19, CYP2D6, and CYP2E1 may contribute to the metabolism of quinine [see Clinical Pharmacology (12.3)].

Antacids: Antacids containing aluminum and/or magnesium may delay or decrease absorption of quinine. Concomitant administration of these antacids with QUALAQUIN should be avoided.

Antiepileptics (AEDs) (carbamazepine, phenobarbital, and phenytoin): Carbamazepine, phenobarbital, and phenytoin are CYP3A4 inducers and may decrease quinine plasma concentrations if used concurrently with QUALAQUIN.

Cholestyramine: In 8 healthy subjects who received quinine sulfate 600 mg with or without 8 grams of cholestyramine resin, no significant difference in quinine pharmacokinetic parameters was seen.

Cigarette Smoking (CYP1A2 inducer): In healthy male heavy smokers, the mean quinine AUC following a single 600 mg dose was 44% lower, the mean Cmax was 18% lower, and the elimination half-life was shorter (7.5 hours versus 12 hours) than in their non-smoking counterparts. However, in malaria patients who received the full 7-day course of quinine therapy, cigarette smoking produced only a 25% decrease in median quinine AUC and a 16.5% decrease in median Cmax, suggesting that the already reduced clearance of quinine in acute malaria could have diminished the metabolic induction effect of smoking. Because smoking did not appear to influence the therapeutic outcome in malaria patients, it is not necessary to increase the dose of quinine in the treatment of acute malaria in heavy cigarette smokers.

Grapefruit juice (P-gp/CYP3A4 inhibitor): In a pharmacokinetic study involving 10 healthy subjects, the administration of a single 600 mg dose of quinine sulfate with grapefruit juice (full-strength or half-strength) did not significantly alter the pharmacokinetic parameters of quinine. QUALAQUIN may be taken with grapefruit juice.

Histamine H2-receptor blockers [cimetidine, ranitidine (nonspecific CYP450 inhibitors)]: In healthy subjects who were given a single oral 600 mg dose of quinine sulfate after pretreatment with cimetidine (200 mg three times daily and 400 mg at bedtime for 7 days) or ranitidine (150 mg twice daily for 7 days), the apparent oral clearance of quinine decreased and the mean elimination half-life increased significantly when given with cimetidine but not with ranitidine. Compared to untreated controls, the mean AUC of quinine increased by 20% with ranitidine and by 42% with cimetidine (p<0.05) without a significant change in mean quinine Cmax. When quinine is to be given concomitantly with a histamine H2-receptor blocker, the use of ranitidine is preferred over cimetidine. Although cimetidine and ranitidine may be used concomitantly with QUALAQUIN, patients should be monitored closely for adverse events associated with quinine.

Isoniazid: Isoniazid 300 mg/day pretreatment for 1 week did not significantly alter the pharmacokinetic parameter values of quinine. Adjustment of QUALAQUIN dosage is not necessary when isoniazid is given concomitantly.

Ketoconazole (CYP3A4 inhibitor): In a crossover study, healthy subjects (N=9) who received a single oral dose of quinine hydrochloride (500 mg) concomitantly with ketoconazole (100 mg twice daily for 3 days) had a mean quinine AUC that was higher by 45% and a mean oral clearance of quinine that was 31% lower than after receiving quinine alone. Although no change in the QUALAQUIN dosage regimen is necessary with concomitant ketoconazole, patients should be monitored closely for adverse reactions associated with quinine.

Macrolide antibiotics (erythromycin, troleandomycin) (CYP3A4 inhibitors): In a crossover study (N=10), healthy subjects who received a single oral 600 mg dose of quinine sulfate with the macrolide antibiotic, troleandomycin (500 mg every 8 hours) exhibited a 87% higher mean quinine AUC, a 45% lower mean oral clearance of quinine, and a 81% lower formation clearance of the main metabolite, 3-hydroxyquinine, than when quinine was given alone.

Erythromycin was shown to inhibit the in vitro metabolism of quinine in human liver microsomes, an observation confirmed by an in vivo interaction study. In a crossover study (N=10), healthy subjects who received a single oral 500 mg dose of quinine sulfate with erythromycin (600 mg every 8 hours for four days) showed a decrease in quinine oral clearance (CL/F), an increase in half-life, and a decreased metabolite (3-hydroxyquinine) to quinine AUC ratio, as compared to when quinine was given with placebo.

Therefore, concomitant administration of macrolide antibiotics such as erythromycin or troleandomycin with QUALAQUIN should be avoided [see Warnings and Precautions (5.3)].

Oral contraceptives (estrogen, progestin): In 7 healthy females who were using single-ingredient progestin or combination estrogen-containing oral contraceptives, the pharmacokinetic parameters of a single 600 mg dose of quinine sulfate were not altered in comparison to those observed in 7 age-matched female control subjects not using oral contraceptives.

Rifampin (CYP3A4 inducer): In patients with uncomplicated P. falciparum malaria who received quinine sulfate 10 mg/kg concomitantly with rifampin 15 mg/kg/day for 7 days (N=29), the median AUC of quinine between days 3 and 7 of therapy was 75% lower as compared to those who received quinine monotherapy. In healthy subjects (N=9) who received a single oral 600 mg dose of quinine sulfate after 2 weeks of pretreatment with rifampin 600 mg/day, the mean quinine AUC and Cmax decreased by 85% and 55%, respectively. Therefore, the concomitant administration of rifampin with QUALAQUIN should be avoided [see Warnings and Precautions (5.4)].

Ritonavir: In healthy subjects who received a single oral 600 mg dose of quinine sulfate with the 15th dose of ritonavir (200 mg every 12 hours for 9 days), there were 4-fold increases in the mean quinine AUC and Cmax, and an increase in the mean elimination half-life (13.4 hours versus 11.2 hours), compared to when quinine was given alone. Therefore, the concomitant administration of ritonavir with QUALAQUIN capsules should be avoided [see also Drug Interactions (7.2)].

Tetracycline: In 8 patients with acute uncomplicated P. falciparum malaria who were treated with oral quinine sulfate (600 mg every 8 hours for 7 days) in combination with oral tetracycline (250 mg every 6 hours for 7 days), the mean plasma quinine concentrations were about two-fold higher than in 8 patients who received quinine monotherapy. Although tetracycline may be concomitantly administered with QUALAQUIN, patients should be monitored closely for adverse reactions associated with quinine sulfate.

Theophylline or aminophylline: In 20 healthy subjects who received multiple doses of QUALAQUIN (648 mg every 8 hours × 7 days) with a single 300 mg oral dose of theophylline, the quinine mean Cmax and AUC were increased by 13% and 14% respectively. Although no change in the QUALAQUIN dosage regimen is necessary with concomitant theophylline or aminophylline, patients should be monitored closely for adverse reactions associated with quinine.

Urinary alkalizers (acetazolamide, sodium bicarbonate): Urinary alkalinizing agents may increase plasma quinine concentrations.

7.2 Effects of Quinine on the Pharmacokinetics of Other Drugs

Results of in vivo drug interaction studies suggest that quinine has the potential to inhibit the metabolism of drugs that are substrates of CYP3A4 and CYP2D6. Quinine inhibits P-gp and has the potential to affect the transport of drugs that are P-gp substrates.

Anticonvulsants (carbamazepine, phenobarbital, and phenytoin): A single 600 mg oral dose of quinine sulfate increased the mean plasma Cmax, and AUC0–24 of single oral doses of carbamazepine (200 mg) and phenobarbital (120 mg) but not phenytoin (200 mg) in 8 healthy subjects. The mean AUC increases of carbamazepine, phenobarbital and phenytoin were 104%, 81% and 4%, respectively; the mean increases in Cmax were 56%, 53%, and 4%, respectively. Mean urinary recoveries of the three antiepileptics over 24 hours were also profoundly increased by quinine. If concomitant administration with carbamazepine or phenobarbital cannot be avoided, frequent monitoring of anticonvulsant drug concentrations is recommended. Additionally, patients should be monitored closely for adverse reactions associated with these anticonvulsants.

Astemizole (CYP3A4 substrate): Elevated plasma astemizole concentrations were reported in a subject who experienced torsades de pointes after receiving three doses of quinine sulfate for nocturnal leg cramps concomitantly with chronic astemizole 10 mg/day. The concurrent use of QUALAQUIN with astemizole and other CYP3A4 substrates with QT prolongation potential (e.g., cisapride, terfenadine, halofantrine, pimozide and quinidine) should also be avoided [see Warnings and Precautions (5.3)].

Atorvastatin (CYP3A4 substrate): Rhabdomyolysis with acute renal failure secondary to myoglobinuria was reported in a patient taking atorvastatin administered with a single dose of quinine. Quinine may increase plasma concentrations of atorvastatin, thereby increasing the risk of myopathy or rhabdomyolysis. Thus, clinicians considering combined therapy of QUALAQUIN with atorvastatin or other HMG-CoA reductase inhibitors ("statins") that are CYP3A4 substrates (e.g., simvastatin, lovastatin) should carefully weigh the potential benefits and risks of each medication. If QUALAQUIN is used concomitantly with any of these statins, lower starting and maintenance doses of the statin should be considered. Patients should also be monitored closely for any signs or symptoms of muscle pain, tenderness, or weakness, particularly during initial therapy. If marked creatine phosphokinase (CPK) elevation occurs or myopathy (defined as muscle aches or muscle weakness in conjunction with CPK values >10 times the upper limit of normal) is diagnosed or suspected, atorvastatin or other statin should be discontinued.

Desipramine (CYP2D6 substrate): Quinine (750 mg/day for 2 days) decreased the metabolism of desipramine in patients who were extensive CYP2D6 metabolizers, but had no effect in patients who were poor CYP2D6 metabolizers. Lower doses (80 mg to 400 mg) of quinine did not significantly affect the pharmacokinetics of other CYP2D6 substrates, namely, debrisoquine, dextromethorphan, and methoxyphenamine. Although clinical drug interaction studies have not been performed, antimalarial doses (greater than or equal to 600 mg) of quinine may inhibit the metabolism of other drugs that are CYP2D6 substrates (e.g., flecainide, debrisoquine, dextromethorphan, metoprolol, paroxetine). Patients taking medications that are CYP2D6 substrates with QUALAQUIN should be monitored closely for adverse reactions associated with these medications.

Digoxin (P-gp substrate): In 4 healthy subjects who received digoxin (0.5 to 0.75 mg/day) during treatment with quinine (750 mg/day), a 33% increase in mean steady state AUC of digoxin and a 35% reduction in the steady state biliary clearance of digoxin were observed compared to digoxin alone. Thus, if QUALAQUIN is administered to patients receiving digoxin, plasma digoxin concentrations should be closely monitored, and the digoxin dose adjusted, as necessary [see Warnings and Precautions (5.7)].

Halofantrine: Although not studied clinically, quinine was shown to inhibit the metabolism of halofantrine in vitro using human liver microsomes. Therefore, concomitant administration of QUALAQUIN is likely to increase plasma halofantrine concentrations [see Warnings and Precautions (5.3)].

Mefloquine: In 7 healthy subjects who received mefloquine (750 mg) at 24 hours before an oral 600 mg dose of quinine sulfate, the AUC of mefloquine was increased by 22% compared to mefloquine alone. In this study, the QTc interval was significantly prolonged in the subjects who received mefloquine and quinine sulfate 24 hours apart. The concomitant administration of mefloquine and QUALAQUIN may produce electrocardiographic abnormalities (including QTc prolongation) and may increase the risk of seizures [see Warnings and Precautions (5.3)].

Midazolam (CYP3A4 substrate): In 23 healthy subjects who received multiple doses of QUALAQUIN 324 mg three times daily × 7 days with a single oral 2 mg dose of midazolam, the mean AUC and Cmax of midazolam and 1-hydroxymidazolam were not significantly affected. This finding indicates that 7-day dosing with QUALAQUIN 324 mg every 8 hours did not induce the metabolism of midazolam.

Neuromuscular blocking agents (pancuronium, succinylcholine, tubocurarine): In one report, quinine potentiated neuromuscular blockade in a patient who received pancuronium during an operative procedure, and subsequently (3 hours after receiving pancuronium) received quinine 1800 mg daily. Quinine may also enhance the neuromuscular blocking effects of succinylcholine and tubocurarine [see Warnings and Precautions (5.5)].

Ritonavir: In healthy subjects who received a single oral 600 mg dose of quinine sulfate with the 15th dose of ritonavir (200 mg every 12 hours for 9 days), the mean ritonavir AUC, Cmax, and elimination half-life were slightly but not significantly increased compared to when ritonavir was given alone. However, due to the significant effect of ritonavir on quinine pharmacokinetics, the concomitant administration of QUALAQUIN capsules with ritonavir should be avoided [see also Drug Interactions (7.1)].

Theophylline or aminophylline (CYP1A2 substrate): In 19 healthy subjects who received multiple doses of QUALAQUIN 648 mg every 8 hours x 7 days with a single 300 mg oral dose of theophylline, the mean theophylline AUC was 10% lower than when theophylline was given alone. There was no significant effect on mean theophylline Cmax. Therefore, if QUALAQUIN is co-administered to patients receiving theophylline or aminophylline, plasma theophylline concentrations should be monitored frequently to ensure therapeutic concentrations.

Warfarin and oral anticoagulants: Cinchona alkaloids, including quinine, may have the potential to depress hepatic enzyme synthesis of vitamin K-dependent coagulation pathway proteins and may enhance the action of warfarin and other oral anticoagulants. Quinine may also interfere with the anticoagulant effect of heparin. Thus, in patients receiving these anticoagulants, the prothrombin time (PT), partial thromboplastin time (PTT), or international normalization ratio (INR) should be closely monitored as appropriate, during concurrent therapy with QUALAQUIN.

7.3 Drug/Laboratory Interactions

Quinine may produce an elevated value for urinary 17-ketogenic steroids when the Zimmerman method is used.

Quinine may interfere with urine qualitative dipstick protein assays as well as quantitative methods (e.g., pyrogallol red-molybdate).

8 USE IN SPECIFIC POPULATIONS

8.1 Pregnancy

TERATOGENIC EFFECTS

Pregnancy Category C

There are extensive published data but few well-controlled studies of QUALAQUIN in pregnant women. Published data on over 1,000 pregnancy exposures to quinine did not show an increase in teratogenic effects over the background rate in the general population; however, the majority of these exposures were not in the first trimester. In developmental and reproductive toxicity studies, central nervous system (CNS) and ear abnormalities and increased fetal deaths occurred in some species when pregnant animals received quinine at doses about 1 to 4 times the human clinical dose. Quinine should be used during pregnancy only if the potential benefit justifies the potential risk to the fetus.

P. falciparum malaria carries a higher risk of morbidity and mortality in pregnant women than in the general population. Pregnant women with P. falciparum malaria have an increased incidence of fetal loss (including spontaneous abortion and stillbirth), preterm labor and delivery, intrauterine growth retardation, low birth weight, and maternal death. Therefore, treatment of malaria in pregnancy is important.

Hypoglycemia, due to increased pancreatic secretion of insulin, has been associated with quinine use, particularly in pregnant women.

Quinine crosses the placenta with measurable blood concentrations in the fetus. In 8 women who delivered live infants 1 to 6 days after starting quinine therapy, umbilical cord plasma quinine concentrations were between 1.0 and 4.6 mg/L (mean 2.4 mg/L) and the mean (±SD) ratio of cord plasma to maternal plasma quinine concentrations was 0.32 ± 0.14. Quinine levels in the fetus may not be therapeutic. If congenital malaria is suspected after delivery, the infant should be evaluated and treated appropriately.

A study from Thailand (1999) of women with P. falciparum malaria who were treated with oral quinine sulfate 10 mg/kg 3 times daily for 7 days at anytime in pregnancy reported no significant difference in the rate of stillbirths at >28 weeks of gestation in women treated with quinine (10 of 633 women [1.6%]) as compared with a control group without malaria or exposure to antimalarial drugs during pregnancy (40 of 2201 women [1.8%]). The overall rate of congenital malformations (9 of 633 offspring [1.4%]) was not different for women who were treated with quinine sulfate compared with the control group (38 of 2201 offspring [1.7%]). The spontaneous abortion rate was higher in the control group (10.9%) than in women treated with quinine sulfate (3.5%) [OR = 3.1; 95% CI 2.1-4.7]. An epidemiologic survey that included 104 mother-child pairs exposed to quinine during the first 4 months of pregnancy, found no increased risk of structural birth defects was seen (2 fetal malformations [1.9%]). Rare and isolated case reports describe deafness and optic nerve hypoplasia in children exposed in utero due to maternal ingestion of high doses of quinine.

In animal developmental studies conducted in multiple animal species, pregnant animals received quinine by the subcutaneous or intramuscular route at dose levels similar to the maximum recommended human dose (MRHD; 32 mg/kg/day) based on body surface area (BSA) comparisons. There were increases in fetal death in utero in rabbits at maternal doses ≥ 100 mg/kg/day and in dogs at ≥ 15 mg/kg/day corresponding to dose levels approximately 0.5 and 0.25 times the MRHD respectively based on BSA comparisons. Rabbit offspring had increased rates of degenerated auditory nerve and spiral ganglion and increased rates of CNS anomalies such as anencephaly and microcephaly at a dose of 130 mg/kg/day corresponding to a maternal dose approximately 1.3 times the MRHD based on BSA comparison. Guinea pig offspring had increased rates of hemorrhage and mitochondrial change in the cochlea at maternal doses of 200 mg/kg corresponding to a dose level of approximately 1.4 times the MRHD based on BSA comparison. There were no teratogenic findings in rats at maternal doses up to 300 mg/kg/day and in monkeys at doses up to 200 mg/kg/day corresponding to doses approximately 1 and 2 times the MRHD respectively based on BSA comparisons.

In a pre- postnatal study in rats, an estimated oral dose of quinine sulfate of 20 mg/kg/day corresponding to approximately 0.1 times the MRHD based on BSA comparison resulted in offspring with impaired growth, lower body weights at birth and during the lactation period, and delayed physical development of teeth eruption and eye opening during the lactation period.

8.2 Labor and Delivery

There is no evidence that quinine causes uterine contractions at the doses recommended for the treatment of malaria. In doses several-times higher than those used to treat malaria, quinine may stimulate the pregnant uterus.

8.3 Nursing Mothers

There is limited information on the safety of quinine in breastfed infants. No toxicity was reported in infants in a single study where oral quinine sulfate (10 mg/kg every 8 hours for 1 to 10 days) was administered to 25 lactating women. It is estimated from this study that breastfed infants would receive less than 2 to 3 mg per day of quinine base (< 0.4% of the maternal dose) via breast milk [see Clinical Pharmacology (12.3)].

Although quinine is generally considered compatible with breastfeeding, the risks and benefits to infant and mother should be assessed. Caution should be exercised when administered to a nursing woman.

If malaria is suspected in the infant, appropriate evaluation and treatment should be provided. Plasma quinine levels may not be therapeutic in infants of nursing mothers receiving QUALAQUIN.

8.4 Pediatric Use

The safety and efficacy of QUALAQUIN in pediatric patients under the age of 16 has not been established.

8.5 Geriatric Use

Clinical studies of quinine sulfate did not include sufficient numbers of subjects aged 65 and over to determine whether they respond to treatment differently from younger subjects. Other reported clinical experience has not identified differences in responses between the elderly and younger patients.

8.6 Renal Impairment

Clearance of quinine is decreased in patients with severe chronic renal failure. The dosage and dosing frequency should be reduced [see Dosage and Administration (2.2), Clinical Pharmacology (12.3)].

8.7 Hepatic Impairment

In patients with severe hepatic impairment (Child-Pugh C), quinine oral clearance (CL/F) is decreased, volume of distribution (Vd/F) is increased, and half-life is prolonged, relative to subjects with normal liver function. Therefore, quinine is not indicated in patients with severe hepatic impairment and alternate therapy should be administered [see Dosage and Administration (2.3) and Clinical Pharmacology (12.3)].

Close monitoring is recommended for patients with mild (Child-Pugh A) or moderate (Child-Pugh B) hepatic impairment, as exposure to quinine may be increased relative to subjects with normal liver function [see Clinical Pharmacology (12.3)].

10 OVERDOSAGE

Quinine overdose can be associated with serious complications, including visual impairment, hypoglycemia, cardiac arrhythmias, and death. Visual impairment can range from blurred vision and defective color perception, to visual field constriction and permanent blindness. Cinchonism occurs in virtually all patients with quinine overdose. Symptoms range from headache, nausea, vomiting, abdominal pain, diarrhea, tinnitus, vertigo, hearing impairment, sweating, flushing, and blurred vision, to deafness, blindness, serious cardiac arrhythmias, hypotension, and circulatory collapse. Central nervous system toxicity (drowsiness, disturbances of consciousness, ataxia, convulsions, respiratory depression and coma) has also been reported with quinine overdose, as well as pulmonary edema and adult respiratory distress syndrome.

Most toxic reactions are dose-related; however, some reactions may be idiosyncratic because of the variable sensitivity of patients to the toxic effects of quinine. A lethal dose of quinine has not been clearly defined, but fatalities have been reported after the ingestion of 2 to 8 grams in adults.

Quinine, like quinidine, has Class I antiarrhythmic properties. The cardiotoxicity of quinine is due to its negative inotropic action, and to its effect on cardiac conduction, resulting in decreased rates of depolarization and conduction, and increased action potential and effective refractory period. ECG changes observed with quinine overdose include sinus tachycardia, PR prolongation, T wave inversion, bundle branch block, an increased QT interval, and a widening of the QRS complex. Quinine's alpha-blocking properties may result in hypotension and further exacerbate myocardial depression by decreasing coronary perfusion. Quinine overdose has been also associated with hypotension, cardiogenic shock, and circulatory collapse, ventricular arrhythmias, including ventricular tachycardia, ventricular fibrillation, idioventricular rhythm, and torsades de pointes, as well as bradycardia, and atrioventricular block [see Warnings and Precautions (5), Clinical Pharmacology (12.3)].

Quinine is rapidly absorbed, and attempts to remove residual quinine sulfate from the stomach by gastric lavage may not be effective. Multiple-dose activated charcoal has been shown to decrease plasma quinine concentrations [see Clinical Pharmacology (12.3)].

Forced acid diuresis, hemodialysis, charcoal column hemoperfusion, and plasma exchange were not found to be effective in significantly increasing quinine elimination in a series of 16 patients.

11 DESCRIPTION

QUALAQUIN (quinine sulfate) is a cinchona alkaloid chemically described as cinchonan-9-ol, 6'-methoxy-, (8α, 9R)-, sulfate (2:1) (salt), dihydrate with a molecular formula of (C20H24N2O2)2•H2SO4•2H2O and a molecular weight of 782.96.

The structural formula of quinine sulfate is:

Quinine sulfate occurs as a white, crystalline powder that darkens on exposure to light. It is odorless and has a persistent very bitter taste. It is only slightly soluble in water, alcohol, chloroform, and ether.

QUALAQUIN is supplied for oral administration as capsules containing 324 mg of the active ingredient quinine sulfate USP, equivalent to 269 mg free base. Inactive ingredients: corn starch, magnesium stearate, and talc.

12 CLINICAL PHARMACOLOGY

12.1 Mechanism of Action

Quinine is an antimalarial agent [see Clinical Pharmacology (12.4)].

12.2 Pharmacodynamics

QTc interval prolongation was studied in a double-blind, multiple dose, placebo- and positive-controlled crossover study in young (N=13, 20 to 39 years) and elderly (N=13, 65 to 78 years) subjects. After 7 days of dosing with QUALAQUIN 648 mg three times daily, the maximum mean (95% upper confidence bound) differences in QTcI from placebo after baseline correction was 27.7 (32.2) ms.

Prolongation of the PR and QRS interval was also noted in subjects receiving QUALAQUIN. The maximum mean (95% upper confidence bound) difference in PR from placebo after baseline-correction was 14.5 (18.0) ms. The maximum mean (95% upper confidence bound) difference in QRS from placebo after baseline-correction was 11.5 (13.3) ms. [see Warnings and Precautions (5.3)].

12.3 Pharmacokinetics

Absorption

The oral bioavailability of quinine is 76 to 88% in healthy adults. Quinine exposure is higher in patients with malaria than in healthy subjects. After a single oral dose of quinine sulfate, the mean quinine Tmax was longer, and mean AUC and Cmax were higher in patients with uncomplicated P. falciparum malaria than in healthy subjects, as shown in Table 1 below.

TABLE 1 Pharmacokinetic Parameters of Quinine in Healthy Subjects and Patients with Uncomplicated P. falciparum Malaria after a Single Dose of Oral Quinine Sulfate Capsules
 | Healthy Subjects (N = 23) Mean ± SD | Uncomplicated P. falciparum Malaria Patients (N = 15) Mean ± SD
Dose (mg/kg) [Quinine Sulfate dose was 648 mg (approximately 8.7 mg/kg) in healthy subjects; and 10 mg/kg in patients with malaria] | 8.7 | 10
Tmax (h) | 2.8 ± 0.8 | 5.9 ± 4.7
Cmax (mcg/mL) | 3.2 ± 0.7 | 8.4
AUC0–12 (mcg*h/mL) | 28.0 | 73.0

QUALAQUIN capsules may be administered without regard to meals. When a single oral 324 mg capsule of QUALAQUIN was administered to healthy subjects (N=26) with a standardized high-fat breakfast, the mean Tmax of quinine was prolonged to about 4.0 hours, but the mean Cmax and AUC0-24h were similar to those achieved when QUALAQUIN capsule was given under fasted conditions [see Dosage and Administration (2.1)].

Distribution

In patients with malaria, the volume of distribution (Vd/F) decreases in proportion to the severity of the infection. In published studies with healthy subjects who received a single oral 600 mg dose of quinine sulfate, the mean Vd/F ranged from 2.5 to 7.1 L/kg.

Quinine is moderately protein-bound in blood in healthy subjects, ranging from 69 to 92%. During active malarial infection, protein binding of quinine is increased to 78 to 95%, corresponding to the increase in α1-acid glycoprotein that occurs with malaria infection.

Intra-erythrocytic levels of quinine are approximately 30 to 50% of the plasma concentration.

Quinine penetrates relatively poorly into the cerebrospinal fluid (CSF) in patients with cerebral malaria, with CSF concentration approximately 2 to 7% of plasma concentration.

In one study, quinine concentrations in placental cord blood and breast milk were approximately 32% and 31%, respectively, of quinine concentrations in maternal plasma. The estimated total dose of quinine secreted into breast milk was less than 2 to 3 mg per day [see Use in Specific Populations (8.1, 8.3)].

Metabolism

Quinine is metabolized almost exclusively via hepatic oxidative cytochrome P450 (CYP) pathways, resulting in four primary metabolites, 3-hydroxyquinine, 2´-quinone, O-desmethylquinine, and 10,11-dihydroxydihydroquinine. Six secondary metabolites result from further biotransformation of the primary metabolites. The major metabolite, 3-hydroxyquinine, is less active than the parent drug.

In vitro studies using human liver microsomes and recombinant P450 enzymes have shown that quinine is metabolized mainly by CYP3A4. Depending on the in vitro experimental conditions, other enzymes, including CYP1A2, CYP2C8, CYP2C9, CYP2C19, CYP2D6, and CYP2E1 were shown to have some role in the metabolism of quinine.

Elimination/Excretion

Quinine is eliminated primarily via hepatic biotransformation. Approximately 20% of quinine is excreted unchanged in urine. Because quinine is reabsorbed when the urine is alkaline, renal excretion of the drug is twice as rapid when the urine is acidic than when it is alkaline.

In various published studies, healthy subjects who received a single oral 600 mg dose of quinine sulfate exhibited a mean plasma clearance ranging from 0.08 to 0.47 L/h/kg (median value: 0.17 L/h/kg) with a mean plasma elimination half-life of 9.7 to 12.5 hours.

In 15 patients with uncomplicated malaria who received a 10 mg/kg oral dose of quinine sulfate, the mean total clearance of quinine was slower (approximately 0.09 L/h/kg) during the acute phase of the infection, and faster (approximately 0.16 L/h/kg) during the recovery or convalescent phase.

Extracorporeal Elimination: Administration of multiple-dose activated charcoal (50 grams administered 4 hours after quinine dosing followed by 3 further doses over the next 12 hours) decreased the mean quinine elimination half-life from 8.2 to 4.6 hours, and increased the mean quinine clearance by 56% (from 11.8 L/h to 18.4 L/h) in 7 healthy adult subjects who received a single oral 600 mg dose of quinine sulfate. Likewise, in 5 symptomatic patients with acute quinine poisoning who received multiple-dose activated charcoal (50 grams every 4 hours), the mean quinine elimination half-life was shortened to 8.1 hours in comparison to a half-life of approximately 26 hours in patients who did not receive activated charcoal [see Overdosage (10)].

In 6 patients with quinine poisoning, forced acid diuresis did not change the half-life of quinine elimination (25.1 ± 4.6 hours vs. 26.5 ± 5.8 hours), or the amount of unchanged quinine recovered in the urine, in comparison to 8 patients not treated in this manner [see Overdosage (10)].

Specific Populations

Pediatric Patients: The pharmacokinetics of quinine in children (1.5 to 12 years old) with uncomplicated P. falciparum malaria appear to be similar to that seen in adults with uncomplicated malaria. Furthermore, as seen in adults, the mean total clearance and the volume of distribution of quinine were reduced in pediatric patients with malaria as compared to the healthy pediatric controls. Table 2 below provides a comparison of the mean ± SD pharmacokinetic parameters of quinine in pediatric patients vs. healthy pediatric controls.

TABLE 2 Quinine Pharmacokinetic Parameters Following the First 10 mg/kg Quinine Sulfate Oral Dose in Healthy Pediatric Controls and Pediatric Patients with Acute Uncomplicated P. falciparum Malaria
 | Healthy Pediatric Controls [age 1.5 to 12 years] (N = 5) Mean ± SD | P. falciparum Malaria Pediatric Patients (N = 15) Mean ± SD
Tmax (h) | 2.0 | 4.0
Cmax (mcg/mL) | 3.4 ± 1.18 | 7.5 ± 1.1
Half-life (h) | 3.2 ± 0.3 | 12.1 ± 1.4
Total CL (L/h/kg) | 0.30 ± 0.04 | 0.06 ± 0.01
Vd (L/kg) | 1.43 ± 0.18 | 0.87 ± 0.12

Geriatric Patients: Following a single oral dose of 600 mg quinine sulfate, the mean AUC was about 38% higher in 8 healthy elderly subjects (65 to 78 years old) than in 12 younger subjects (20 to 35 years old). The mean Tmax and Cmax were similar in elderly and younger subjects after a single oral dose of quinine sulfate 600 mg. The mean oral clearance of quinine was significantly decreased, and the mean elimination half-life was significantly increased in elderly subjects compared with younger subjects (0.06 vs. 0.08 L/h/kg, and 18.4 hours vs. 10.5 hours, respectively). Although there was no significant difference in the renal clearance of quinine between the two age groups, elderly subjects excreted a larger proportion of the dose in urine as unchanged drug than younger subjects (16.6% vs. 11.2%).

After a single 648 mg dose or at steady state, following quinine sulfate 648 mg given three times daily for 7 days, no difference in the rate and extent of absorption or clearance of quinine was seen between 13 elderly subjects (65 to 78 years old) and 14 young subjects (20 to 39 years old). The mean elimination half-life was 20% longer in the elderly subjects (24.0 hours) than in younger subjects (20.0 hours). The steady state Cmax (±SD) and AUC0-8 (±SD) for healthy volunteers are 6.8 ± 1.24 mcg/mL and 48.8 ± 9.15 mcg*h/mL, respectively, following 7 days of oral quinine sulfate 648 mg three times daily. The steady state pharmacokinetic parameters in healthy elderly subjects were similar to the pharmacokinetic parameters in healthy young subjects.

Renal Impairment: Following a single oral 600 mg dose of quinine sulfate in otherwise healthy subjects with severe chronic renal failure not receiving any form of dialysis (mean serum creatinine = 9.6 mg/dL), the median AUC was higher by 195% and the median Cmax was higher by 79% than in subjects with normal renal function (mean serum creatinine = 1 mg/dL). The mean plasma half-life in subjects with severe chronic renal impairment was prolonged to 26 hours compared to 9.7 hours in the healthy controls. Computer assisted modeling and simulation indicates that in patients with malaria and severe chronic renal failure, a dosage regimen consisting of one loading dose of 648 mg QUALAQUIN followed 12 hours later by a maintenance dosing regimen of 324 mg every 12 hours will provide adequate systemic exposure to quinine [see Dosage and Administration (2.2)]. The effects of mild and moderate renal impairment on the pharmacokinetics and safety of quinine sulfate are not known.

Negligible to minimal amounts of circulating quinine in the blood are removed by hemodialysis or hemofiltration. In subjects with chronic renal failure (CRF) on hemodialysis, only about 6.5% of quinine is removed in 1 hour. Plasma quinine concentrations do not change during or shortly after hemofiltration in subjects with CRF [see Overdosage (10)].

Hepatic Impairment: In otherwise healthy subjects with mild hepatic impairment (Child-Pugh A; N=10), who received a single 500 mg dose of quinine sulfate, there was no significant difference in quinine pharmacokinetic parameters or exposure to the primary metabolite, 3-hydroxyquinine as compared to healthy controls (N=10). In otherwise healthy subjects with moderate hepatic impairment (Child-Pugh B; N=9) who received a single oral 600 mg dose of quinine sulfate, the mean AUC increased by 55% without a significant change in mean Cmax, as compared to healthy volunteer controls (N=6). In subjects with hepatitis, the absorption of quinine was prolonged, the elimination half-life was increased, the apparent volume of distribution was higher, but there was no significant difference in weight-adjusted clearance. Therefore, in patients with mild to moderate hepatic impairment, dosage adjustment is not needed, but patients should be monitored closely for adverse effects of quinine [see Use in Specific Populations (8.7)].

In subjects with severe hepatic impairment (Child-Pugh C; N=10), quinine oral clearance (CL/F) was reduced as was formation of the primary 3-hydroxyquinine metabolite. Volume of distribution (Vd/F) was higher and the plasma elimination half-life was increased. Therefore, quinine is not indicated in this population and alternate therapy should be administered [see Dosage and Administration (2.3)].

12.4 Microbiology

Mechanism of Action

Quinine inhibits nucleic acid synthesis, protein synthesis, and glycolysis in Plasmodium falciparum and can bind with hemazoin in parasitized erythrocytes. However, the precise mechanism of the antimalarial activity of quinine sulfate is not completely understood.

Activity In Vitro and In Vivo

Quinine sulfate acts primarily on the blood schizont form of P. falciparum. It is not gametocidal and has little effect on the sporozoite or pre-erythrocytic forms.

Drug Resistance

Strains of P. falciparum with decreased susceptibility to quinine can be selected in vivo. P. falciparum malaria that is clinically resistant to quinine has been reported in some areas of South America, Southeast Asia, and Bangladesh.

13 NONCLINICAL TOXICOLOGY

13.1 Carcinogenesis, Mutagenesis, Impairment of Fertility

Carcinogenesis

Carcinogenicity studies of quinine have not been conducted.

Mutagenesis

Genotoxicity studies of quinine were positive in the Ames bacterial mutation assay with metabolic activation and in the sister chromatid exchange assay in mice. The sex-linked recessive lethal test performed in Drosophila, the in vivo mouse micronucleus assay, and the chromosomal aberration assay in mice and Chinese hamsters were negative.

Impairment of Fertility

Published studies indicate that quinine produces testicular toxicity in mice at a single intraperitoneal dose of 300 mg/kg corresponding to a dose of approximately 0.75 times the maximum recommended human dose (MRHD; 32 mg/kg/day) and in rats at an intramuscular dose of 10 mg/kg/day, 5 days/week, for 8 weeks corresponding to a daily dose of approximately 0.05 times the MRHD based on body surface area (BSA) comparisons. The findings include atrophy or degeneration of the seminiferous tubules, decreased sperm count and motility, and decreased testosterone levels in the serum and testes. There was no effect on testes weight in studies of oral doses of up to 500 mg/kg/day in mice and 700 mg/kg/day in rats (approximately 1.2 and 3.5 times the MRHD respectively based on BSA comparisons). In a published study in 5 men receiving 600 mg of quinine TID for one week, sperm motility was decreased and percent sperm with abnormal morphology was increased; sperm count and serum testosterone were unaffected.

14 CLINICAL STUDIES

Quinine has been used worldwide for hundreds of years in the treatment of malaria. Thorough searches of the published literature identified over 1300 references to the treatment of malaria with quinine, and from these, 21 randomized, active-controlled studies were identified which evaluated oral quinine monotherapy or combination therapy for treatment of uncomplicated P. falciparum malaria. Over 2900 patients from malaria-endemic areas were enrolled in these studies, and more than 1400 patients received oral quinine. The following conclusions were drawn from review of these studies:

In areas where multi-drug resistance of P. falciparum is increasing, such as Southeast Asia, cure rates with 7 days of oral quinine monotherapy were at least 80%; while cure rates for 7 days of oral quinine combined with an antimicrobial agent (tetracycline or clindamycin) were greater than 90%. In areas where multi-drug resistance of the parasite was not as widespread, cure rates with 7 days of quinine monotherapy ranged from 86 to 100%. Cure was defined as initial clearing of parasitemia within 7 days without recrudescence by day 28 after treatment initiation. P. falciparum malaria that is clinically resistant to quinine has been reported in some areas of South America, Southeast Asia, and Bangladesh, and quinine may not be as effective in those areas.

Completion of a 7-day oral quinine treatment regimen may be limited by drug intolerance, and shorter courses (3 days) of quinine combination therapy have been used. However, the published data from randomized, controlled clinical trials for shorter regimens of oral quinine in conjunction with tetracycline, doxycycline, or clindamycin for treatment of uncomplicated P. falciparum malaria is limited, and these shorter course combination regimens may not be as effective as the longer regimens.

16 HOW SUPPLIED / STORAGE AND HANDLING

16.1 How Supplied

QUALAQUIN capsules USP, 324 mg are available as clear/clear capsules imprinted AR 102:

Bottles of 30 | NDC 13310-153-07
Bottles of 100 | NDC 13310-153-01
Bottles of 500 | NDC 13310-153-05
Bottles of 1000 | NDC 13310-153-10

16.2 Storage

Store at 20° to 25°C (68° to 77°F).

[See USP Controlled Room Temperature]

Dispense in a tight container as defined in the USP.

17 PATIENT COUNSELING INFORMATION

See FDA-approved Medication Guide (17.2)

17.1 Dosing Instructions

Patients should be instructed to:

- Take all of the medication as directed.
- Take no more of the medication than the amount prescribed.
- Take with food to minimize possible gastrointestinal irritation.

If a dose is missed, patients should also be instructed not to double the next dose. If more than 4 hours has elapsed since the missed dose, the patient should wait and take the next dose as previously scheduled.

MEDICATION GUIDE

QUALAQUIN®
(kwol-a-kwin)

(Quinine sulfate) Capsules

Read the Medication Guide that comes with QUALAQUIN® before you start taking it and each time you get a refill. There may be new information. This Medication Guide does not take the place of talking to your healthcare provider about your medical condition or treatment. You and your healthcare provider should talk about QUALAQUIN® when you start taking it and at regular checkups. QUALAQUIN® is not approved for the treatment of night-time leg cramps.

What is the most important information I should know about QUALAQUIN®?

QUALAQUIN® used to treat or prevent leg cramps may cause serious side effects or even death.

- QUALAQUIN® may cause your blood cell (platelet) count to drop causing serious bleeding problems. In some people, serious kidney problems can happen.
- QUALAQUIN® may cause problems with your heart rhythm that can lead to death.
- QUALAQUIN® may cause serious allergic reactions.

Call your healthcare provider right away if you have:

- easy bruising
- severe nose bleed
- blood in urine or stool
- bleeding gums
- appearance of unusual purple, brown or red spots on your skin (bleeding under your skin)
- rash
- hives
- severe itching

- severe flushing
- swelling of your face
- trouble breathing
- chest pain
- rapid heartbeat
- irregular heart rhythm
- weakness
- sweating
- nervousness

Taking QUALAQUIN® with some other medicines can increase the chance of serious side effects. Tell your healthcare provider if you take any other medicines.

Certain medicines can cause the blood levels of QUALAQUIN® to be too high or too low in your body. It is important for you to tell your healthcare provider about all the medicines you take, including prescription and non-prescription medicines, vitamins and herbal supplements.

QUALAQUIN® and other medicines may affect each other causing serious side effects or death. Even medicines that you may take for a short period of time, such as antibiotics, can mix in your blood with QUALAQUIN® and cause serious side effects or death. Do not start taking a new medicine without telling your healthcare provider or pharmacist.

What is QUALAQUIN®?

QUALAQUIN® is a prescription medication used to treat malaria (uncomplicated) caused by the parasite Plasmodium falciparum.

QUALAQUIN® is Not approved to:

- Prevent malaria
- Treat severe or complicated malaria
- Prevent or treat night-time leg cramps

It is not known if QUALAQUIN® is safe and works in children younger than 16 years old.

Who should not take QUALAQUIN®?

Do not take QUALAQUIN® if you have:

- certain heart rhythm problems (atrial fibrillation) or abnormal electrocardiogram (ECG) (QT prolongation).
- low levels of an enzyme called Glucose-6-phosphate dehydrogenase (G6PD).
- an autoimmune disease (myasthenia gravis) that leads to muscle weakness.
- had allergic reactions to quinine, quinidine, or mefloquine (Lariam®).
- had serious side effects to quinine (QUALAQUIN®), such as low platelets, which are necessary for your blood to clot.
- an inflammation of the nerve important for vision (optic neuritis).

What should I tell my healthcare provider before starting QUALAQUIN®?

Before you take QUALAQUIN®, tell your healthcare provider if you:

- Have heart problems.
- Have kidney problems.
- Have liver problems.
- Have any other medical condition.
- Are pregnant or could be pregnant. Treatment of malaria is important because it can be a serious disease for a pregnant woman and her unborn baby. Your healthcare provider can tell you more about the benefits and risks of taking this medication during pregnancy. Low blood sugar (hypoglycemia) can be seen in pregnant women while taking QUALAQUIN®. This can include sweating, weakness, nausea, vomiting, or confusion. You and your healthcare provider can decide if QUALAQUIN® is right for you.
- Are breast-feeding. Small amounts of QUALAQUIN® can pass into your breast milk. You and your healthcare provider can decide if you should breastfeed while taking QUALAQUIN®.

Tell your healthcare provider about all the medicines you take, including prescription medicines, vitamins and herbal supplements.

How should I take QUALAQUIN®?

- Take QUALAQUIN® exactly as your healthcare provider tells you to take it.
- Your healthcare provider will tell you how many QUALAQUIN® capsules to take and when to take them.
- To lower the chance of stomach upset, take QUALAQUIN® with food.
- Finish all the QUALAQUIN® that is prescribed even if you feel better. Do not stop taking the medication without talking to your healthcare provider.
- Do not take more than the amount prescribed. Do not take more than 2 capsules at one time or more than 3 doses in one day. If you take more than the prescribed dose, call your healthcare provider right away.
- If you forget to take QUALAQUIN®, do not double the next dose. If it has been more than 4 hours since the missed dose, just wait and take the regular dose at the next scheduled time. Call your healthcare provider if you are not sure what to do.
- If you take too much QUALAQUIN®, call your healthcare provider or go to the nearest emergency room right away.

Call your healthcare provider right away if:

- If you feel worse, or if you do not start feeling better within 1 or 2 days of starting to take QUALAQUIN®.
- If your fever comes back after finishing treatment with QUALAQUIN®.

What are the possible side effects of QUALAQUIN®?

QUALAQUIN® may cause serious side effects.

- See "What is the most important information I should know about QUALAQUIN®" section.
- Low blood sugar (hypoglycemia). This can include sweating, weakness, nausea, vomiting, or confusion.

Common side effects with QUALAQUIN® include:

- headache
- sweating
- flushing
- nausea
- ringing in your ears
- diarrhea
- deafness

- hearing loss
- dizziness (vertigo)
- blurred vision
- changes in how you see color
- vomiting
- stomach pain
- blindness

Tell your healthcare provider if you have any side effect that bothers you or that does not go away.

These are not all of the possible side effects of QUALAQUIN®. For more information, ask your healthcare provider or pharmacist.

Call your doctor for medical advice about side effects. You may report side effects to FDA at 1-800-FDA-1088.

How should I store QUALAQUIN®?

- Keep the capsules in a tightly closed container.
- Do not refrigerate or freeze.
- Store at 20°C to 25°C (68ºF to 77°F).

Keep QUALAQUIN® and all medicines out of the reach of children.

General Information about QUALAQUIN®

Medicines are sometimes prescribed for purposes other than those listed in a Medication Guide. Do not use QUALAQUIN® for a condition for which it was not prescribed. Do not give QUALAQUIN® to other people, even if they have the same symptoms that you have. It may harm them.

This Medication Guide summarizes the most important information about QUALAQUIN®. If you would like more information, talk with your healthcare provider. You can ask your healthcare provider or pharmacist for information about QUALAQUIN® that is written for healthcare professionals.

For more information, go to www.QUALAQUIN.com or call 1-888-351-3786.

What are the ingredients in QUALAQUIN®?

Active Ingredients: Quinine Sulfate, USP
Inactive Ingredients: Corn starch, magnesium stearate, talc

This Medication Guide has been approved by the U.S. Food and Drug Administration.

Manufactured for:
AR SCIENTIFIC, INC.
Philadelphia, PA 19124 USA
by:
MUTUAL PHARMACEUTICAL COMPANY, INC.
Philadelphia, PA 19124 USA

Rev 23, April 2013

PRINCIPAL DISPLAY PANEL - 324 mg Capsule Bottle Label

100 CAPSULES
NDC 13310-153-01

QUALAQUIN®
quinine sulfate
capsules USP

324 mg

DISPENSE THE ACCOMPANYING
MEDICATION GUIDE TO EACH PATIENT

AR
SCIENTIFIC

Rx only